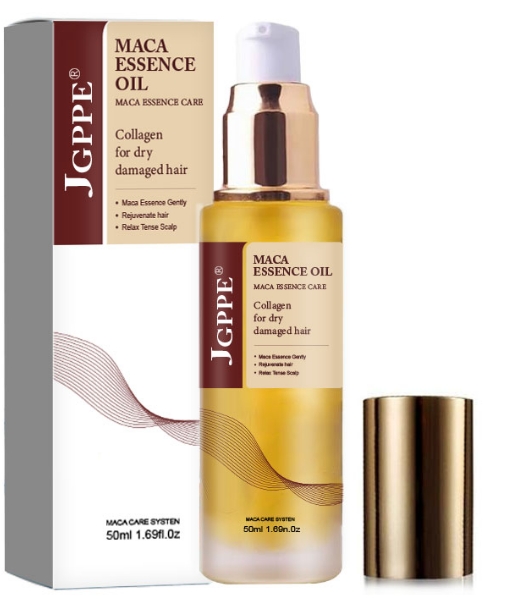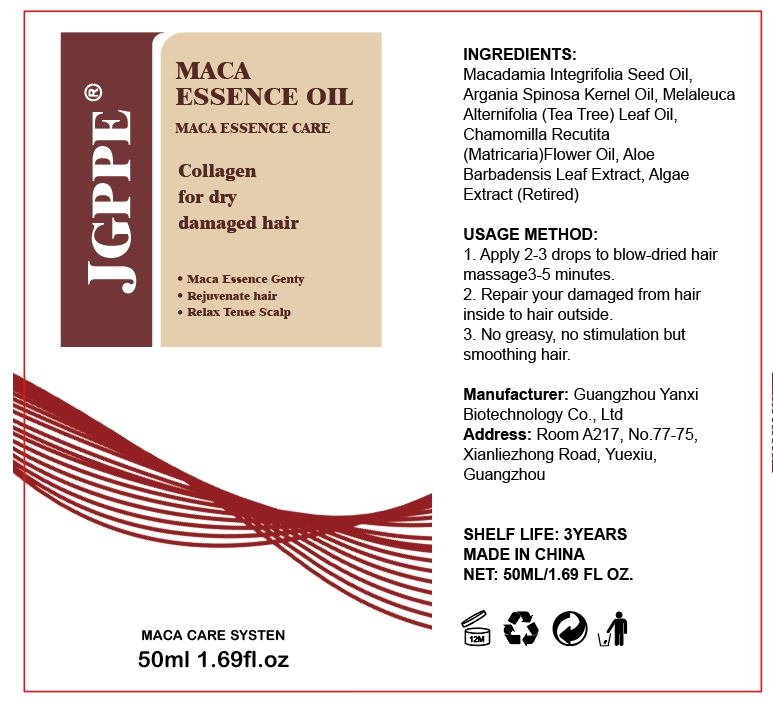 DRUG LABEL: MACA ESSENCE CARE
NDC: 84025-035 | Form: LIQUID
Manufacturer: Guangzhou Yanxi Biotechnology Co., Ltd
Category: otc | Type: HUMAN OTC DRUG LABEL
Date: 20240429

ACTIVE INGREDIENTS: MACADAMIA INTEGRIFOLIA WHOLE 5 mg/50 mL; ARGANIA SPINOSA WHOLE 2 mg/50 mL
INACTIVE INGREDIENTS: WATER

DOSAGE AND ADMINISTRATION

use as a normal hair oil

Keep out of reach of children.

INACTIVE INGREDIENT

Aqua

Keep out of reach of children.

PURPOSE

repair damaged hair

INDICATIONS AND USAGE

Apply to affected area twice per day on hair. Use continuously for 2-3 weeks for best results.